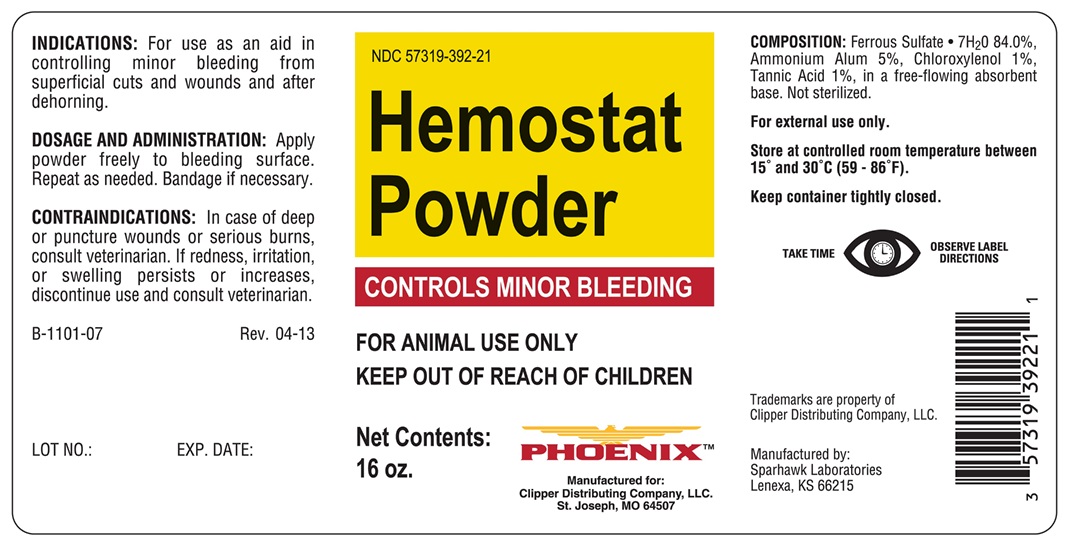 DRUG LABEL: Hemostat
NDC: 57319-392 | Form: POWDER
Manufacturer: Clipper Distributing Company, LLC
Category: animal | Type: OTC ANIMAL DRUG LABEL
Date: 20170626

ACTIVE INGREDIENTS: FERROUS SULFATE 76.6 g/454 g

Hemostat Powder

INDICATIONS AND USAGE

CONTROLS MINOR BLEEDING

FOR ANIMAL USE ONLY

KEEP OUT OF REACH OF CHILDREN

INDICATIONS

For use as an aid in controlling minor bleeding from superficial cuts and wounds and after dehorning.

DOSAGE AND ADMINISTRATION

Apply powder freely to bleeding surface. Repeat as needed. Bandage if necessary.

CONTRAINDICATIONS

In case of deep or puncture wounds or serious burns, consult veterinarian. If redness, irritation, or swelling persists or increases, discontinue use and consult veterinarian.

COMPOSITION

Ferrous Sulfate • 7H2O 84.0%, Ammonium Alum 5%, Chloroxylenol 1%, Tannic Acid 1%, In a free-flowing absorbent base. Not sterilized

For external use only.

STORAGE AND HANDLING

Store at controlled room temperature between 15° and 30°C (59°-86°F)

Keep container tightly closed.

TAKE TIME OBSERVE LABEL DIRECTIONS